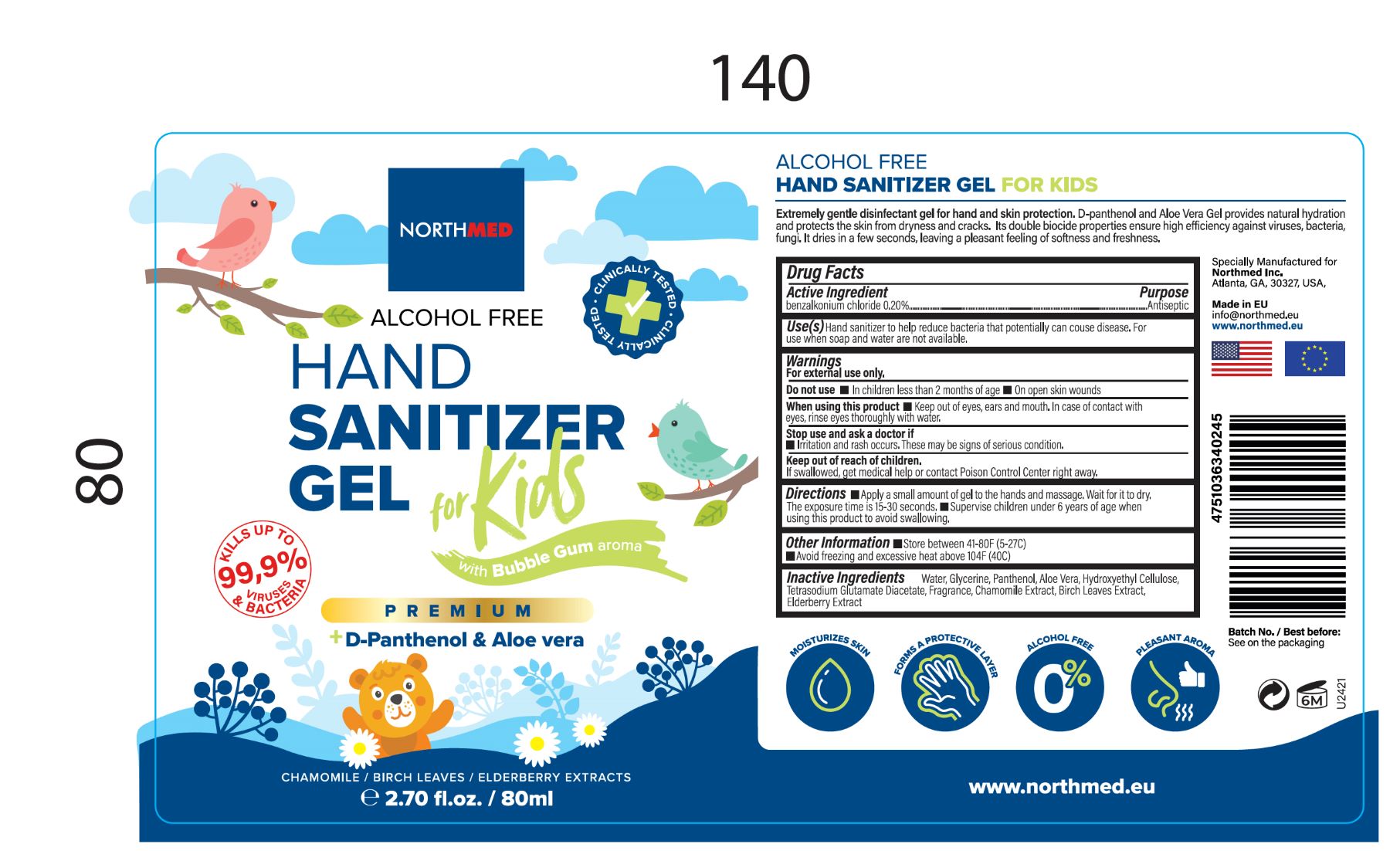 DRUG LABEL: Hand Sanitizer
NDC: 78522-101 | Form: GEL
Manufacturer: Northmed
Category: otc | Type: HUMAN OTC DRUG LABEL
Date: 20210316

ACTIVE INGREDIENTS: BENZALKONIUM CHLORIDE 2 mg/80 mL
INACTIVE INGREDIENTS: FRAGRANCE FLORAL ORC0902236; WATER; TETRASODIUM GLUTAMATE DIACETATE; GLYCERIN; ALOE VERA LEAF; HYDROXYETHYL CELLULOSE, UNSPECIFIED; BIRCH TRITERPENES; PANTHENOL; CHAMOMILE FLOWER OIL

gel for kids, 80ml

Active ingredient

benzalkonium chloride 0.20%

Purpose

Antiseptic

Use(s)

Use(s). Hand sanitizer to help reduce bacteria that potentially can cause disease. For use when soap and water are not available.

WARNINGS

For external use only.

Do not use: in children less than 2 months of age; on open skin wounds.

When using this product: keep out of eyes, ears and mouth. In case of contact with eyes, rinse eyes thoroughly with water.

Stop Use

Stop use and ask a doctor if irritation or rash occurs. These may be signs of a serious condition.

Keep out of reach of children. If swallowed, get medical help or contact Poison Control Center right away.

Directions

Directions. Apply a small amount of gel to the hands and massage. Wait for it to dry. The exposure time is 15-30 seconds. Supervise children under 6 years of age when using this product to avoid swallowing.

Storage.

Store between 41-80F (5-27C). Avoid freezing and excessive heat above 104F (40C).

Inactive Ingredients

Inactive Ingredients.Water. glycerin, panthenol, aloe vera, hydroxyethyl cellulose, tetrasodium glutamate diacetate, fragrance, chamomile extract, birch leaf extract, elderberry extract.